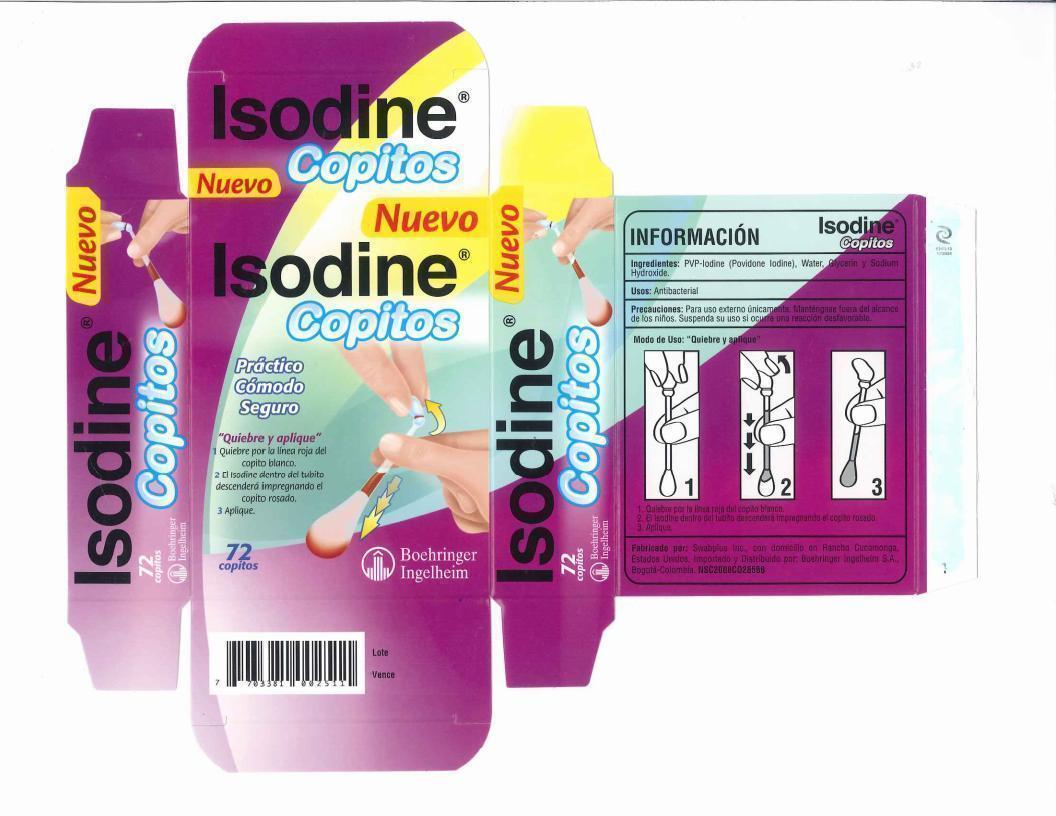 DRUG LABEL: Isodine Copitos
                
                
NDC: 65734-511 | Form: SOLUTION
Manufacturer: Swabplus Inc.
Category: otc | Type: HUMAN OTC DRUG LABEL
Date: 20150216

ACTIVE INGREDIENTS: Povidone-Iodine 10 mg/1 mL
INACTIVE INGREDIENTS: Glycerin; Sodium Hydroxide; WATER

Isodine Copitos

Drug Facts Active ingredient

Povidone iodine 10%, equal to 1% available Iodine

Purpose

Antiseptic

Uses First aid to help prevent infection due to minor cuts, scrapes and burns.

Keep out of reach of children

if swallowed, get medical help of contact a Poison Control Center right away.

Directions

- Hold the swab vertically, with the color ring tip upwards, Hold n the center of the tube with one hand at the color ring with the other.
- Gently snap the tip with the color ring, Formula inside the tube flows down and fills the opposite tip.
- Apply the product to the affected area.
- Discard swab after use.

Warnings

For external use only. Keep out of eyes and ear canal. Non-Sterile. Discontinue use if irritation.
Do not use. If you are sensitive to Iodine. Longer than one week unless directed by a doctor.
Stop use and ask a doctor. If you have deep or puncture wounds, or serious burns. redness, irritation, swelling or pain continue or increas., infedtion occurs.

Administration

For adults and children 2 and older: for minor wounds, burns and infections, apply directly to affected area. May be covered with a bandage.
Children under 2 years of age: Do not use, consult a doctor.
Other information: Store art room temperature, Avoid direct sunlight, excessive heat and moisture.

Inactive ingredients

Glycerin, water

Manufacturer Statement

Patented and manufactured by Swabplus Inc. Rancho Cucamonga, CA 91730 USA Made in USA

Imported and Distributed by Boehringer Ingelheim

Package and Labeling

Image of iodine carton label